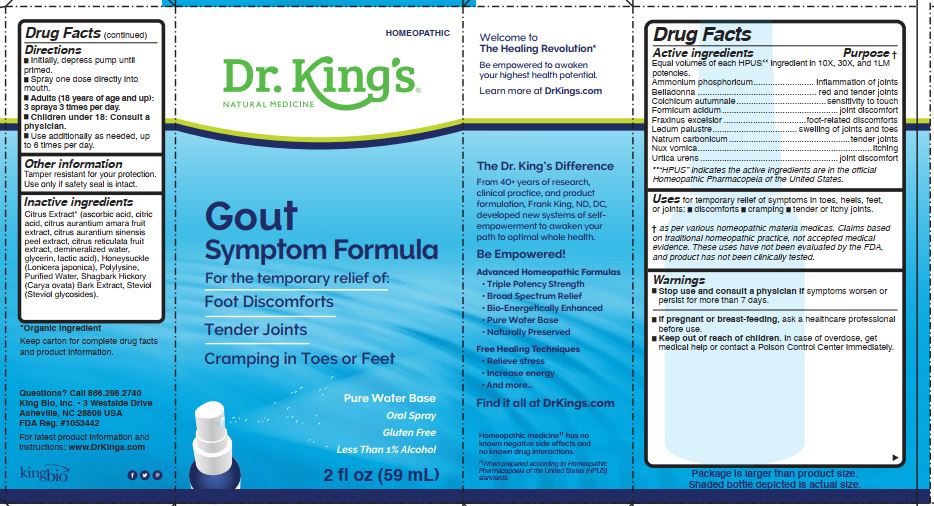 DRUG LABEL: Gout Symptom Formula
NDC: 57955-2826 | Form: LIQUID
Manufacturer: King Bio Inc.
Category: homeopathic | Type: HUMAN OTC DRUG LABEL
Date: 20241120

ACTIVE INGREDIENTS: AMMONIUM PHOSPHATE, DIBASIC 10 [hp_X]/59 mL; ATROPA BELLADONNA 10 [hp_X]/59 mL; COLCHICUM AUTUMNALE BULB 10 [hp_X]/59 mL; FORMIC ACID 10 [hp_X]/59 mL; FRAXINUS EXCELSIOR LEAF 10 [hp_X]/59 mL; RHODODENDRON TOMENTOSUM LEAFY TWIG 10 [hp_X]/59 mL; SODIUM CARBONATE 10 [hp_X]/59 mL; STRYCHNOS NUX-VOMICA SEED 10 [hp_X]/59 mL; URTICA URENS WHOLE 10 [hp_X]/59 mL
INACTIVE INGREDIENTS: ASCORBIC ACID; CITRIC ACID MONOHYDRATE; CITRUS AURANTIUM FRUIT OIL; ORANGE PEEL; CITRUS RETICULATA FRUIT OIL; WATER; GLYCERIN; LACTIC ACID, UNSPECIFIED FORM; LONICERA JAPONICA FLOWER; POLYEPSILON-LYSINE (4000 MW); CARYA OVATA BARK; STEVIOL

Gout Symptom Formula

Directions

Initially, depress pump until
primed.

Spray one dose directly into
mouth.

Adults (18 years of age and up):
3 sprays 3 times per day.

Children under 18: Consult a
physician.

Use additionally as needed, up
to 6 times per day.

Reference image: Gout.jpg

Other information

Tamper resistant for your protection.

Use only if safety seal is intact.

Keep carton for complete drug facts and product information.

Questions? Call 866.298.2740

King Bio, Inc. 3 Westside Drive

Asheville, NC 2806 USA

FDA Reg. #1053442

For latest product information and instructions: www.DrKings.com

Reference image: Gout.jpg

Inactive Ingredients

Citrus Extract (ascorbic acid, citric acid, citrus aurantium amara fruit extract, citrus aurantium sinensis peel extract, citrus reticulata fruit extact, demineralized water, glycerin, lactic acid), Honeysuckle (Lonicera japonica), Polylysine, Purified Water, Shagbark Hickory (Carya Ovata) Bark Extract, Steviol (Steviol Glycosides).

Reference image: Gout.jpg

Active ingredients

Equal volumes of each HPUS ingredient in 10X, 30X, and 1LM
potencies.

Ammonium phosphoricum, Belladonna, Colchicum autumnale, Formicum acidum, Fraxinus excelsior, Ledum palustre, Natrum carbonicum,
Nux vomica, Urtica urens.

HPUS” indicates the active ingredients are in the official
Homeopathic Pharmacopeia of the United States.

Reference image: Gout.jpg

Uses

For temporary relief of symptoms in toes, heels, feet,
or joints:

discomforts

cramping

tender or itchy joints

As per various homeopathic materia medicas. Claims based
on traditional homeopathic practice, not accepted medical
evidence. These uses have not been evaluated by the FDA,
and product has not been clinically tested.

Reference image: Gout.jpg

Warnings

Stop use and consult a physician if symptoms worsen or
persist for more than 7 days.

If pregnant or breast-feeding, ask a healthcare professional
before use.
Keep out of reach of children.

In case of overdose, get medical help or contact a Poison Control Center immediately.

Reference image: Gout.jpg

Keep out of reach of children.

In case of overdose, get medical help or contact a Poison Control Center immediately.

Reference image: Gout.jpg

PURPOSE

Equal volumes of each HPUS ingredient in 10X, 30X, and 1LM
potencies.

Ammonium phosphoricum......................... inflammation of joints
Belladonna ................................................. red and tender joints
Colchicum autumnale.....................................sensitivity to touch
Formicum acidum................................................ joint discomfort
Fraxinus excelsior ..................................foot-related discomforts
Ledum palustre................................... swelling of joints and toes
Natrum carbonicum ..................................................tender joints
Nux vomica........................................................................itching
Urtica urens ......................................................... joint discomfort

HPUS” indicates the active ingredients are in the official
Homeopathic Pharmacopeia of the United States.

Reference image: Gout.jpg